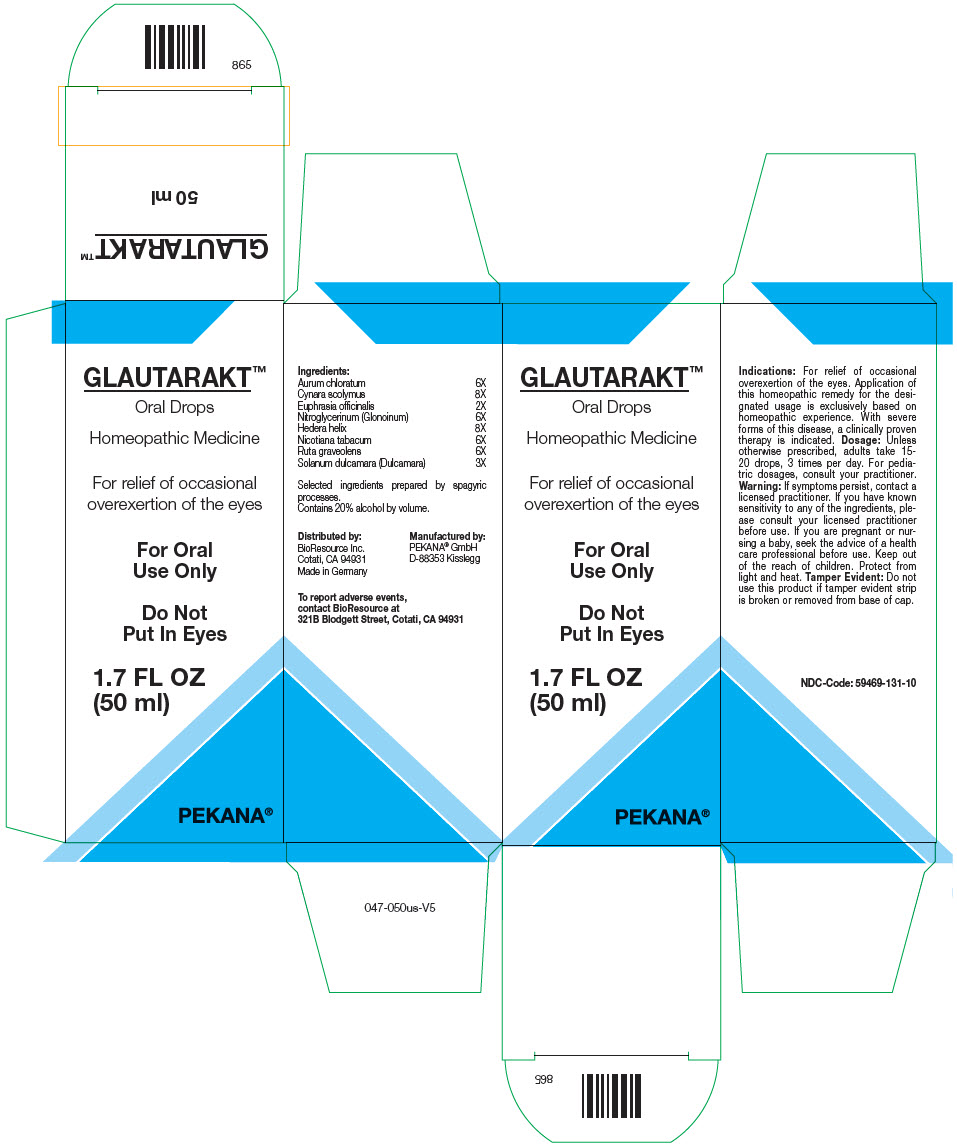 DRUG LABEL: GLAUTARAKT
NDC: 59469-131 | Form: SOLUTION/ DROPS
Manufacturer: PEKANA Naturheilmittel GmbH
Category: homeopathic | Type: HUMAN OTC DRUG LABEL
Date: 20221215

ACTIVE INGREDIENTS: Gold Trichloride 6 [hp_X]/50 mL; Solanum dulcamara Top 3 [hp_X]/50 mL; Euphrasia Stricta 2 [hp_X]/50 mL; Nitroglycerin 6 [hp_X]/50 mL; Hedera helix Flowering Twig 8 [hp_X]/50 mL; Ruta graveolens Flowering Top 6 [hp_X]/50 mL; Tobacco Leaf 6 [hp_X]/50 mL; Cynara scolymus Whole 8 [hp_X]/50 mL
INACTIVE INGREDIENTS: Water; Alcohol

GLAUTARAKT™

ACTIVE INGREDIENT

Ingredients:
Aurum chloratum | 6X
Cynara scolymus | 8X
Euphrasia officinalis | 2X
Nitroglycerinum (Glonoinum) | 6X
Hedera helix | 8X
Nicotiana tabacum | 6X
Ruta graveolens | 6X
Solanum dulcamara (Dulcamara) | 3X

Selected ingredients prepared by spagyric processes.

INACTIVE INGREDIENT

Contains 20% alcohol by volume.

Indications

PURPOSE

For relief of occasional overexertion of the eyes. Application of this homeopathic remedy for the designated usage is exclusively based on homeopathic experience. With severe forms of this disease, a clinically proven therapy is indicated.

Dosage

Unless otherwise prescribed, adults take 15-20 drops, 3 times per day. For pediatric dosages, consult your practitioner.

Warning

ASK DOCTOR

If symptoms persist, contact a licensed practitioner. If you have known sensitivity to any of the ingredients, please consult your licensed practitioner before use. If you are pregnant or nursing a baby, seek the advice of a health care professional before use.

Keep out of the reach of children.

STORAGE AND HANDLING

Protect from light and heat.

Tamper Evident

Do not use this product if tamper evident strip is broken or removed from base of cap.

QUESTIONS

To report adverse events, contact BioResource at 321B Blodgett Street, Cotati, CA 94931

Distributed by:
BioResource Inc.
Cotati, CA 94931

Manufactured by:
PEKANA® GmbH
D-88353 Kisslegg

PRINCIPAL DISPLAY PANEL - 50 ml Bottle Box

GLAUTARAKT™

Oral Drops

Homeopathic Medicine

For relief of occasional
overexertion of the eyes

For Oral
Use Only

Do Not
Put In Eyes

1.7 FL OZ
(50 ml)

PEKANA®